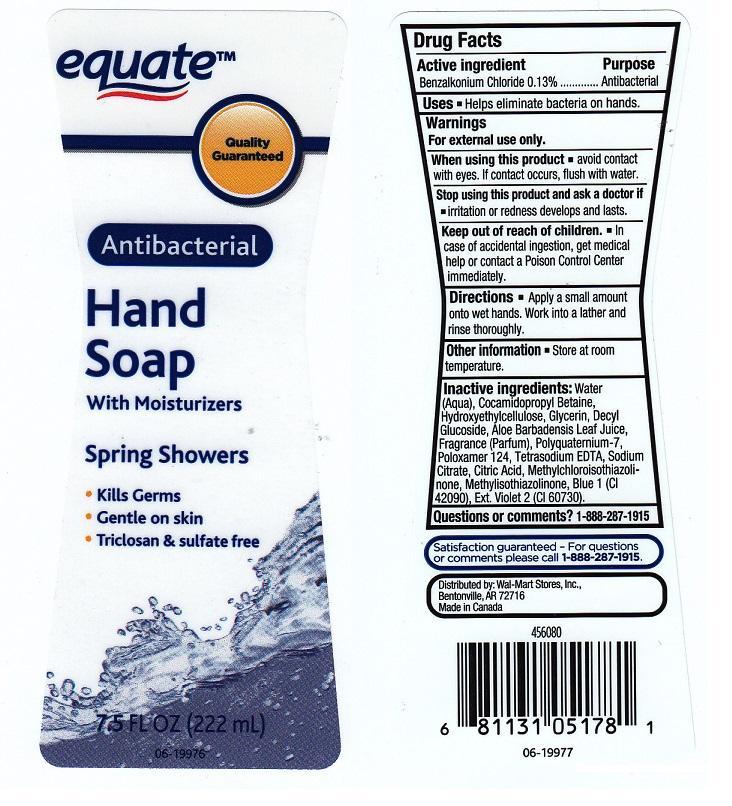 DRUG LABEL: EQUATE
NDC: 49035-724 | Form: LIQUID
Manufacturer: WAL-MART STORES INC
Category: otc | Type: HUMAN OTC DRUG LABEL
Date: 20140818

ACTIVE INGREDIENTS: BENZALKONIUM CHLORIDE 1.3 mg/1 mL
INACTIVE INGREDIENTS: WATER; COCAMIDOPROPYL BETAINE; HYDROXYETHYL CELLULOSE (5000 CPS AT 1%); GLYCERIN; DECYL GLUCOSIDE; ALOE VERA LEAF; POLYQUATERNIUM-7 (70/30 ACRYLAMIDE/DADMAC; 1600000 MW); POLOXAMER 124; EDETATE SODIUM; SODIUM CITRATE; CITRIC ACID MONOHYDRATE; METHYLCHLOROISOTHIAZOLINONE; METHYLISOTHIAZOLINONE; FD&C BLUE NO. 1; EXT. D&C VIOLET NO. 2

DRUG FACTS

ACTIVE INGREDIENT

BENZALKONIUM CHLORIDE 0.13%

PURPOSE

ANTIBACTERIAL

USES

HELPS ELIMINATE BACTERIA ON HANDS

WARNINGS

FOR EXTERNAL USE ONLY

WHEN USING THIS PRODUCT

AVOID CONTACT WITH EYES. IF CONTACT OCCURS, FLUSH WITH WATER

STOP USING THIS PRODUCT AND ASK A DOCTOR IF

IRRITATION OR REDNESS DEVELOPS AND LASTS

KEEP OUT OF REACH OF CHILDREN

IN CASE OF ACCIDENTAL INGESTION, GET MEDICAL HELP OR CONTACT A POISON CONTROL CENTER IMMEDIATELY

DIRECTIONS

APPLY A SMALL AMOUNT ONTO WET HANDS. WORK INTO A LATHER AND RINSE THOROUGHLY

OTHER INFORMATION

STORE AT ROOM TEMPERATURE

INACTIVE INGREDIENTS

WATER (AQUA), COCAMIDOPROPYL BETAINE, HYDROXYETHYLCELLULOSE, GLYCERIN, DECYL GLUCOSIDE, ALOE BARBADENSIS LEAF JUICE, FRAGRANCE (PARFUM), POLYQUATERNIUM-7, POLOXAMER 124, TETRASODIUM EDTA, SODIUM CITRATE, CITRIC ACID, METHYLCHLOROISOTHIAZOLINONE, METHYLISOTHIAZOLINONE, BLUE 1 (CI 42090), EXT. VIOLET 2 (CI 60730)

QUESTIONS OR COMMENTS?

1-888-287-1915